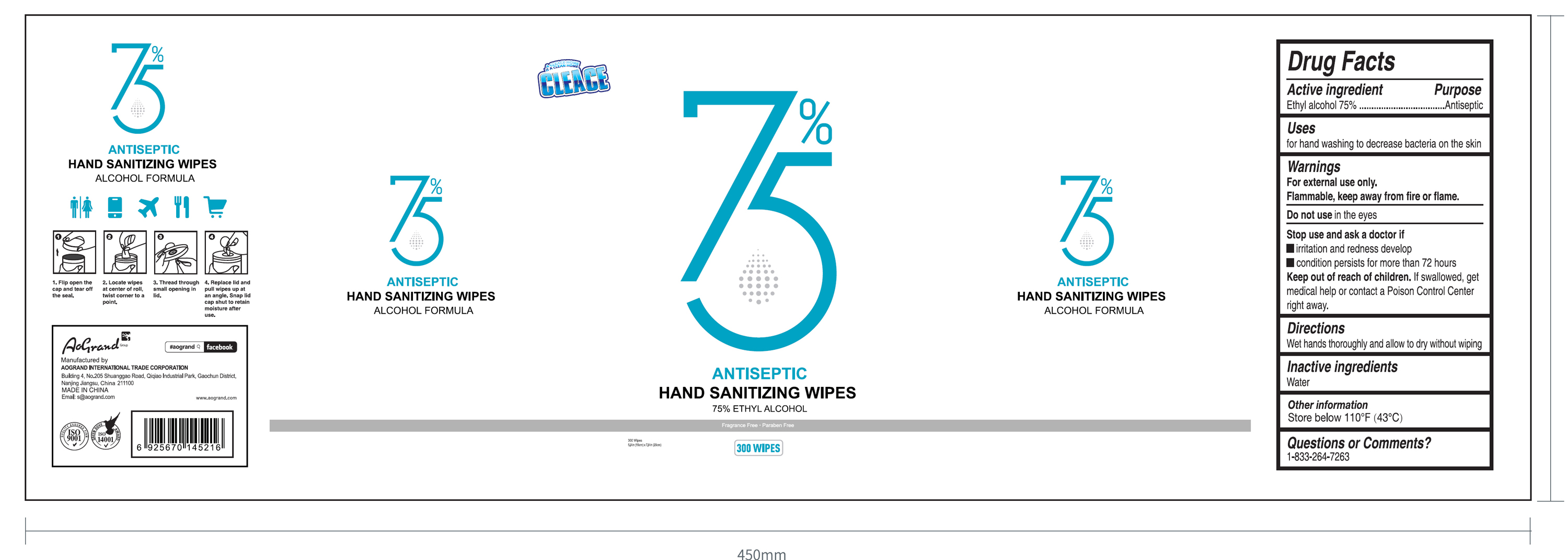 DRUG LABEL: CLEACE 75% Ethyl Alcohol Antiseptic Hand Sanitizing Wipes
NDC: 74621-028 | Form: CLOTH
Manufacturer: Aogrand International Trade Corporation
Category: otc | Type: HUMAN OTC DRUG LABEL
Date: 20230211

ACTIVE INGREDIENTS: ALCOHOL 75 mL/100 g
INACTIVE INGREDIENTS: WATER

CLEACE 75% Ethyl Alcohol Antiseptic Hand Sanitizing Wipes (300 wipes)

Active ingredient

Ethyl Alcohol 75% Purpose: Antiseptic

Purpose

Antiseptic

Uses

For hand washing to decrease bacteria on the skin

Warnings

For external use only.

Flammable. Keep away from fire or flame.

Do not use

in the eyes

Stop use and ask a doctor if

- irritation and redness develop
- condition persists for more than 72 hours

Keep out of reach of children.

If swallowed, get medical help or contact a Poison Control Center right away.

Directions

Wet hands thoroughly and allow to dry without wiping

Inactive ingredients

Water

Other information

Store below 110F (43C)

Questions or Comments?

1-833-264-7263

Package Label - Principal Display Panel

300PCS NDC: 74621-028-01

A CLEACE HOME

IS A CLEAN HOME

CLEACE

75%

Antiseptic

Hand Sanitizer wipes

75% Ethyl Alcohol

Fragrance Free

Paraben Free

300 Wipes

5.9 in (15cm) x 7.9 in (20cm)

300 WIPES